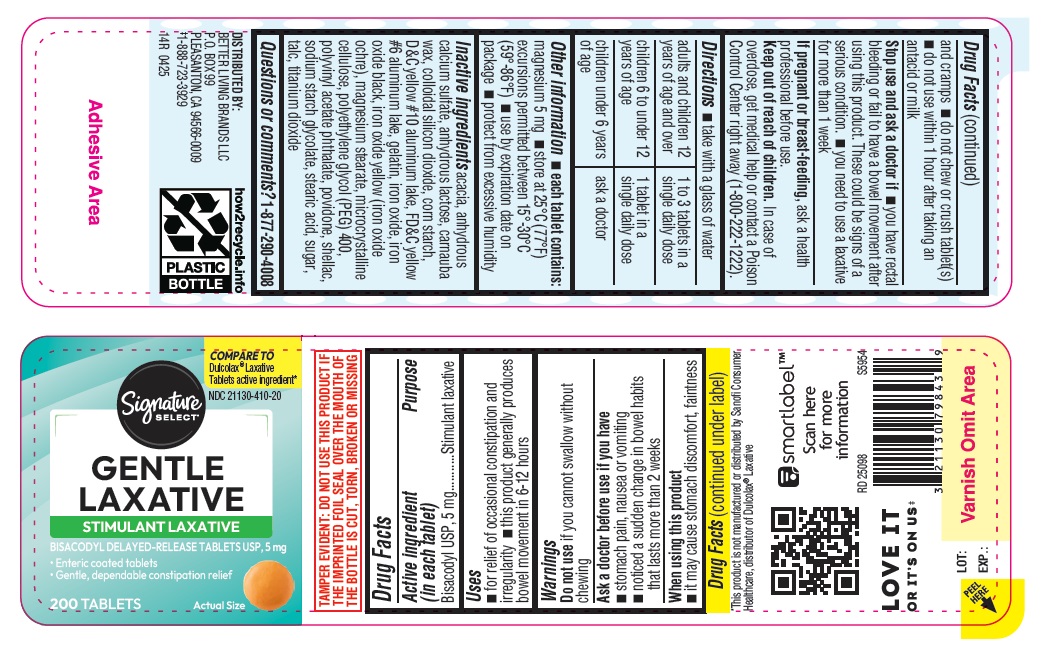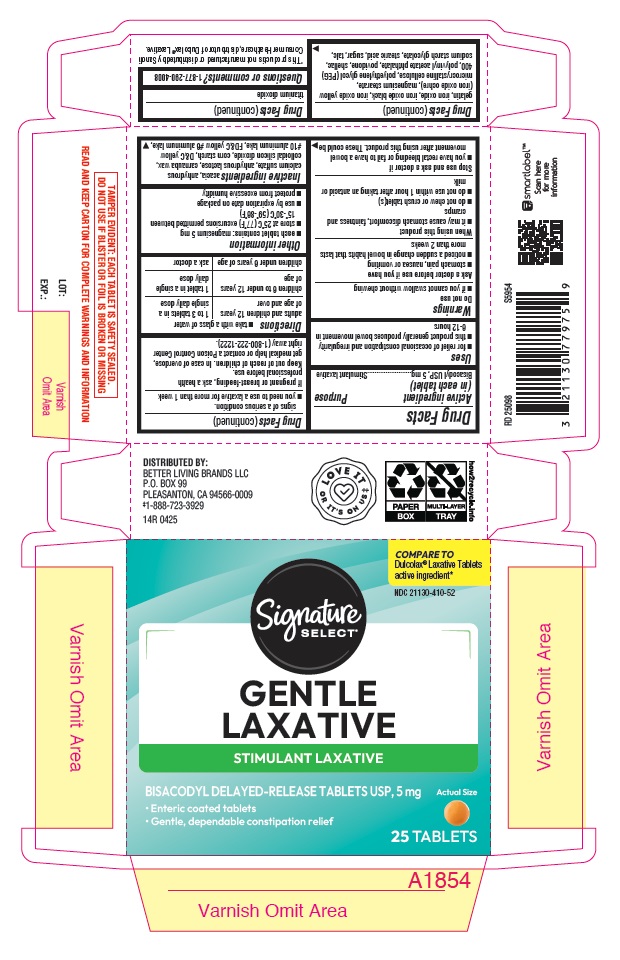 DRUG LABEL: Gentle Laxative
NDC: 21130-410 | Form: TABLET, DELAYED RELEASE
Manufacturer: BETTER LIVING BRANDS LLC.
Category: otc | Type: HUMAN OTC DRUG LABEL
Date: 20250913

ACTIVE INGREDIENTS: BISACODYL 5 mg/1 1
INACTIVE INGREDIENTS: FERRIC OXIDE RED; CALCIUM SULFATE ANHYDROUS; D&C YELLOW NO. 10 ALUMINUM LAKE; FERROSOFERRIC OXIDE; FERRIC OXIDE YELLOW; MAGNESIUM STEARATE; POLYETHYLENE GLYCOL 400; POLYVINYL ACETATE PHTHALATE; SHELLAC; SODIUM STARCH GLYCOLATE TYPE A CORN; STEARIC ACID; CARNAUBA WAX; FD&C YELLOW NO. 6 ALUMINUM LAKE; MICROCRYSTALLINE CELLULOSE; SUCROSE; TALC; TITANIUM DIOXIDE; ANHYDROUS LACTOSE; ACACIA; GELATIN; POVIDONE; SILICON DIOXIDE; STARCH, CORN

14R_Albertsons_21130-410_Bisacodyl Delayed Release Tablets 5 mg

Active ingredient (in each tablet)

Bisacodyl USP, 5 mg

Purpose

Stimulant laxative

Uses

- for relief of occasional constipation and irregularity
- this product generally produces bowel movement in 6-12 hours

Warnings

Do not use

- if you cannot swallow without chewing

Ask a doctor before use if you have

- stomach pain, nausea or vomiting
- noticed a sudden change in bowel habits that lasts more than 2 weeks

When using this product

- it may cause stomach discomfort, faintness and cramps
- do not chew or crush tablet(s)
- do not use within 1 hour after taking an antacid or milk

Stop use and ask a doctor if

- you have rectal bleeding or fail to have a bowel movement after using this product. These could be signs of a serious condition.
- you need to use a laxative for more than 1 week

PREGNANCY OR BREAST FEEDING

If pregnant or breast-feeding, ask a health professional before use.

Keep out of reach of children. In case of overdose, get medical help or contact a Poison Control Center right away (1-800-222-1222).

Directions

- take with a glass of water

adults and children 12 years of age and over | 1 to 3 tablets in a single daily dose
children 6 to under 12 years of age | 1 tablet in a single daily dose
children under 6 years of age | ask a doctor

Other information

- each tablet contains: magnesium 5 mg
- store at 25°C (77°F) excursions permitted between 15°-30°C (59°-86°F)
- use by expiration date on package
- protect from excessive humidity

INACTIVE INGREDIENT

Inactive ingredients acacia, anhydrous calcium sulfate, anhydrous lactose, carnauba wax, colloidal silicon dioxide, corn starch, D&C yellow #10 aluminum lake, FD&C yellow #6 aluminum lake, gelatin, iron oxide, iron oxide black, iron oxide yellow (iron oxide ochre), magnesium stearate, microcrystalline cellulose, polyethylene glycol (PEG) 400, polyvinyl acetate phthalate, povidone, shellac, sodium starch glycolate, stearic acid, sugar, talc, titanium dioxide

Questions or comments? 1-877-290-4008

PACKAGE LABEL

Bisacodyl tablets 25ct IFC

Bisacodyl tablets 200ct label